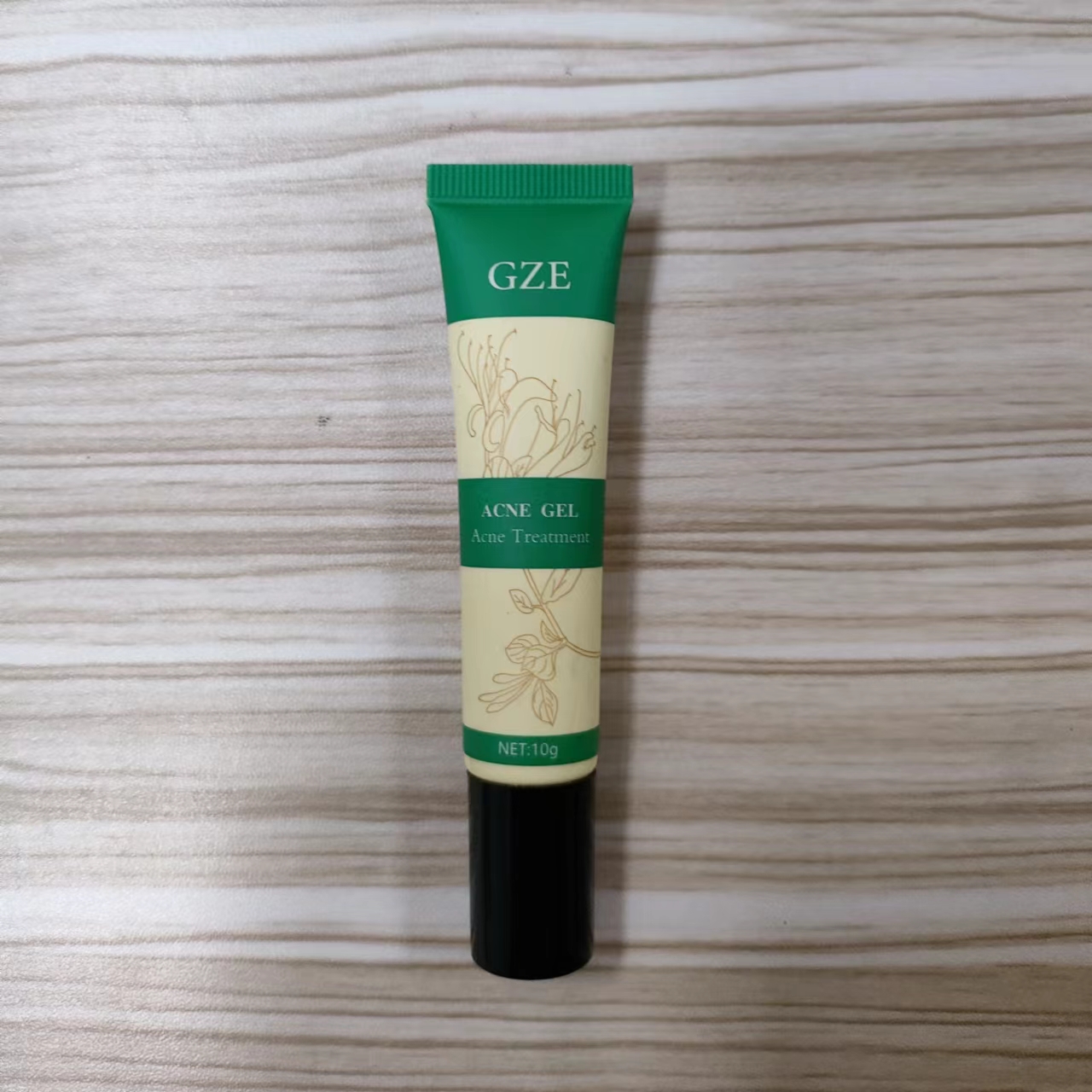 DRUG LABEL: GZE Acne Gel
NDC: 74458-028 | Form: GEL
Manufacturer: Guangzhou Yilong Cosmetics Co., Ltd
Category: otc | Type: HUMAN OTC DRUG LABEL
Date: 20241011

ACTIVE INGREDIENTS: LACTIC ACID 5 g/100 g; TEA TREE OIL 12 g/100 g; LONICERA JAPONICA FLOWER 10 g/100 g; CHRYSANTHELLUM INDICUM TOP 2 g/100 g
INACTIVE INGREDIENTS: TOCOPHEROL; ALLANTOIN; WATER; DIAZOLIDINYL UREA

GZE ACNE GEL

ASK DOCTOR

Lactic Acid 5% Chrysanthellum Indicum Top 2% Lonicera Japonica Flower 10% Tea Tree Oil 12%

INACTIVE INGREDIENT

Aqua

Tocopherol

Allantoin

Diazolidinyl Urea

PURPOSE

Acne treatment.

WARNINGS

For external use only.

Stop use and ask a doctor if rash occurs.

When using this product keep out of eyes. Rinse with water to remove.

INDICATIONS AND USAGE

Apply a dime-sized amount of gel to your finger and massage gently onto any pimples or spots. Leave it on for a few hours or over nightbefore washing your face. The redness and swelling should decrease.

Keep out of reach of children. If swallowed, get medical help or contact a Poison Control Center right away.

DOSAGE AND ADMINISTRATION

Apply a dime-sized amount of gel to your finger and massage gently onto any pimples or spots. Leave it on for a few hours or over nightbefore washing your face. The redness and swelling should decrease.